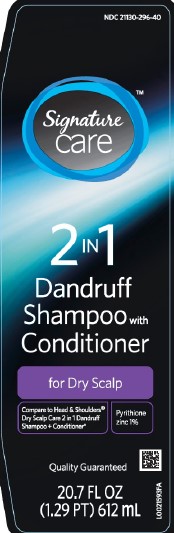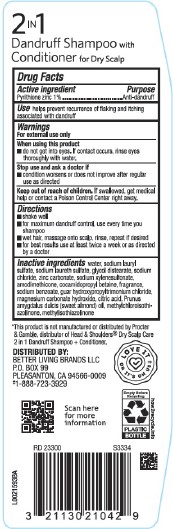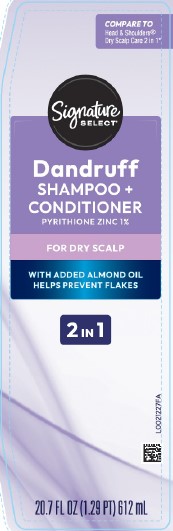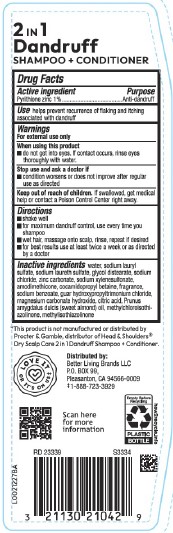 DRUG LABEL: Dry Scalp Care
NDC: 21130-296 | Form: SHAMPOO
Manufacturer: Better Living Brands, LLC
Category: otc | Type: HUMAN OTC DRUG LABEL
Date: 20260223

ACTIVE INGREDIENTS: PYRITHIONE ZINC 10 mg/1 mL
INACTIVE INGREDIENTS: SODIUM LAURYL SULFATE; SODIUM LAURETH-3 SULFATE; GLYCOL DISTEARATE; SODIUM CHLORIDE; ZINC CARBONATE; SODIUM XYLENESULFONATE; AMODIMETHICONE (800 CST); COCAMIDOPROPYL BETAINE; SODIUM BENZOATE; GUAR HYDROXYPROPYLTRIMONIUM CHLORIDE (1.7 SUBSTITUENTS PER SACCHARIDE); MAGNESIUM CARBONATE HYDROXIDE; CITRIC ACID MONOHYDRATE; ALMOND OIL; METHYLCHLOROISOTHIAZOLINONE; METHYLISOTHIAZOLINONE; WATER

Signature Care_Signature Select 296.007/296AT-AW
Dry Scalp 2 In 1 Dandruff Shampoo

Claims

2 in 1

Dandruff

SHAMPOO + CONDITIONER

Active ingredient

Pyrithione zinc 1%

Purpose

Anti-Dandruff

Use

helps prevent recurrence of flaking and itching associated with dandruff

Warnings

For external use only

When using this product

- do not get into eyes. If contact occurs, rinse eyes thoroughly with water.

Stop use and ask a doctor if

- condition worsens or does not improve after regular use as directed

Keep out of reach of children.

If swallowed, get medical help or contact a Poison Control Center right away.

Directions

- shake well
- for maximum dandruff control, use every time you shampoo
- wet hair, massage onto scalp, rinse, repeat if desired
- for best results use at least twice a week or as directed by a doctor

Inactive ingredients

water, sodium lauryl sulfate, sodium laureth sulfate, glycol distearate, sodium chloride, zinc carbonate, sodium xylenesulfonate, amodimethicone, cocamidopropyl betaine, fragrance, sodium benzoate, guar hydroxypropyltrimonium chloride, magnesium carbonate hydroxide, citric acid, Prunus amygdalus dulcis (sweet almond) oil, methylchloroisothiazolinone, methylisothiazolinone

Disclaimer

*This product is not manufactured or distributed by Procter & Gamble, the distributor of Head & Shoulders®Dry Scalp Care 2in1 Dandruff Shampoo + Conditioner.

Adverse reaction

DISTRIBUTED BY

BETTER LIVING BRANDS LLC

P.O. BOX 99

PLEASANTON, CA 94566-0009

‡1-888-723-3929

LOVE IT OR IT'S ON US‡

Scan here for more information

Empty Before Recycling

PLASTIC BOTTLE

how2recycle.info

Principal display panel

NDC 21130-296-40

Signature Care™

2 in 1

Dandruff

Shampoo with Conditioner

for Dry Scalp

Compare to Head & Shoulders®Dry Scalp Care 2 in 1 Dandruff Shampoo + Conditioner*

Pyrithione zinc 1%

Quality Guaranteed

20.7 FL OZ (1.29 PT) 612 mL

Principal display panel

COMPARE TO Head & Shoulders® Dry Scalp Care 2 in 1*

Signature SELECT®

Dandruff SHAMPOO + CONDITIONER

PYRITHIONE ZINC 1%

FOR DRY SCALP

WITH ADDED ALMOND OIL

HELPS PREVENT FLAKES

2IN1

20.7 FL OZ (1.29 PT) 612 mL